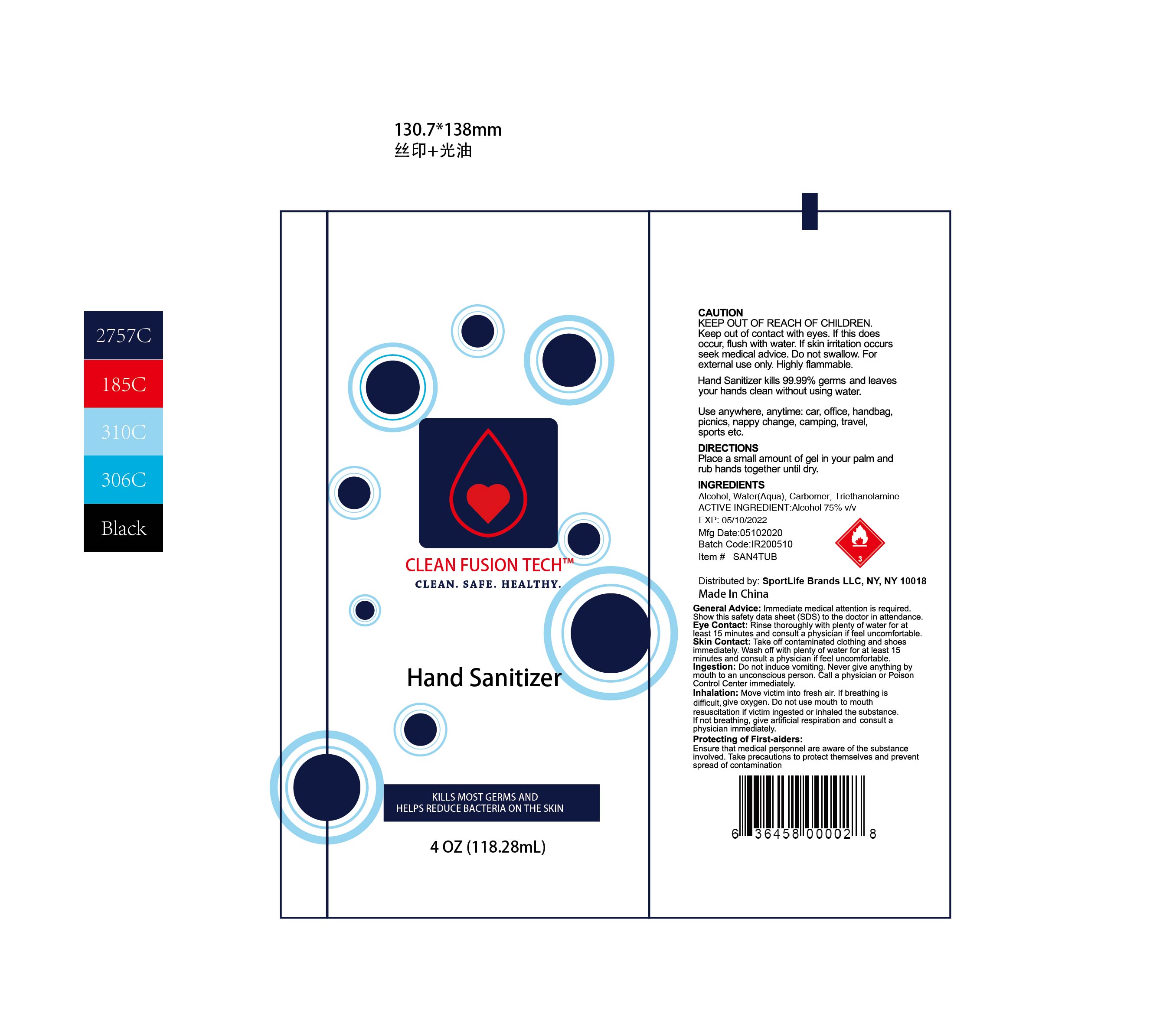 DRUG LABEL: HAND SANITISER
NDC: 74440-024 | Form: GEL
Manufacturer: Jiangxi Iris Chemical Co.,Ltd
Category: otc | Type: HUMAN OTC DRUG LABEL
Date: 20200512

ACTIVE INGREDIENTS: ALCOHOL 75 mL/100 mL
INACTIVE INGREDIENTS: WATER; TROLAMINE; CARBOMER HOMOPOLYMER, UNSPECIFIED TYPE

HAND SANITISER

ACTIVE INGREDIENT

Alcohol 75% v/v

Use

anywhere,anytime:car,office, handbag,picnics, nappy change,camping, travel,sports etc.

KEEP OUT OF REACH OF CHILDREN

Keep out of contact with eyes.If this does occur,flush with water.If skin irritation occurs

seek medical advice.Do not swallow.For external use only.Highly flammable.

DIRECTIONS

Place a small amount of gel in your palm and rub hands together until dry.

Inactive ingredients

Water(Aqua),Carbomer,Triethanolamine.